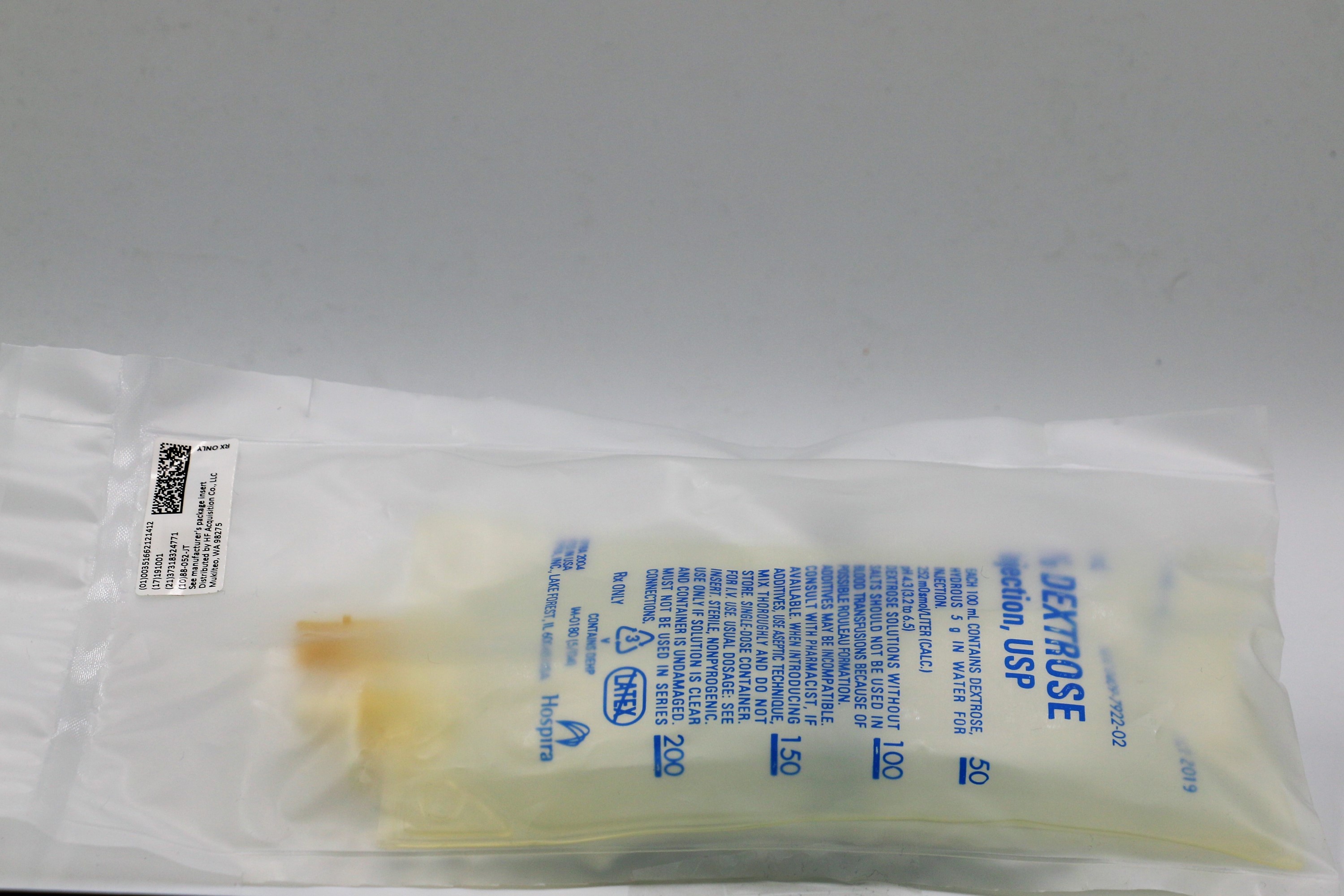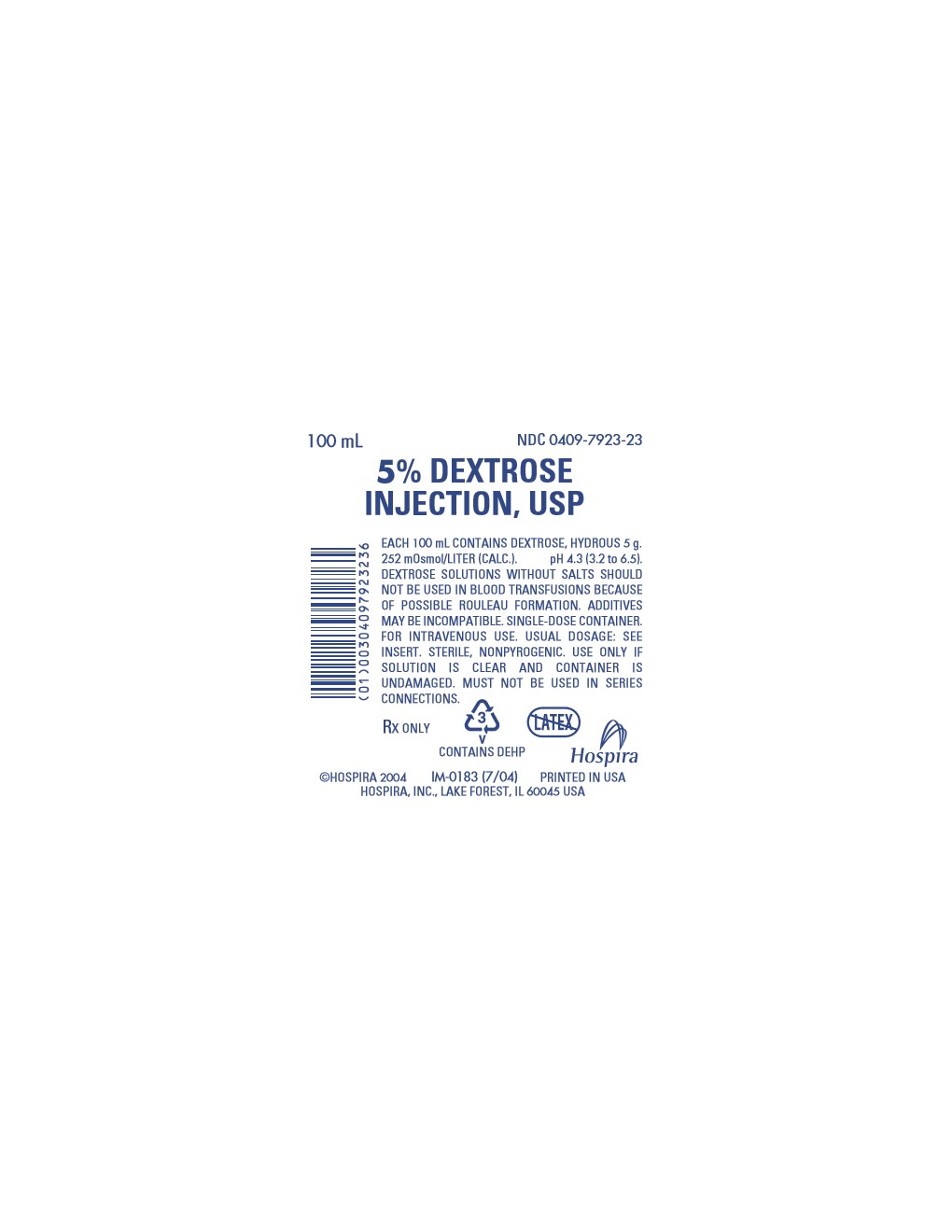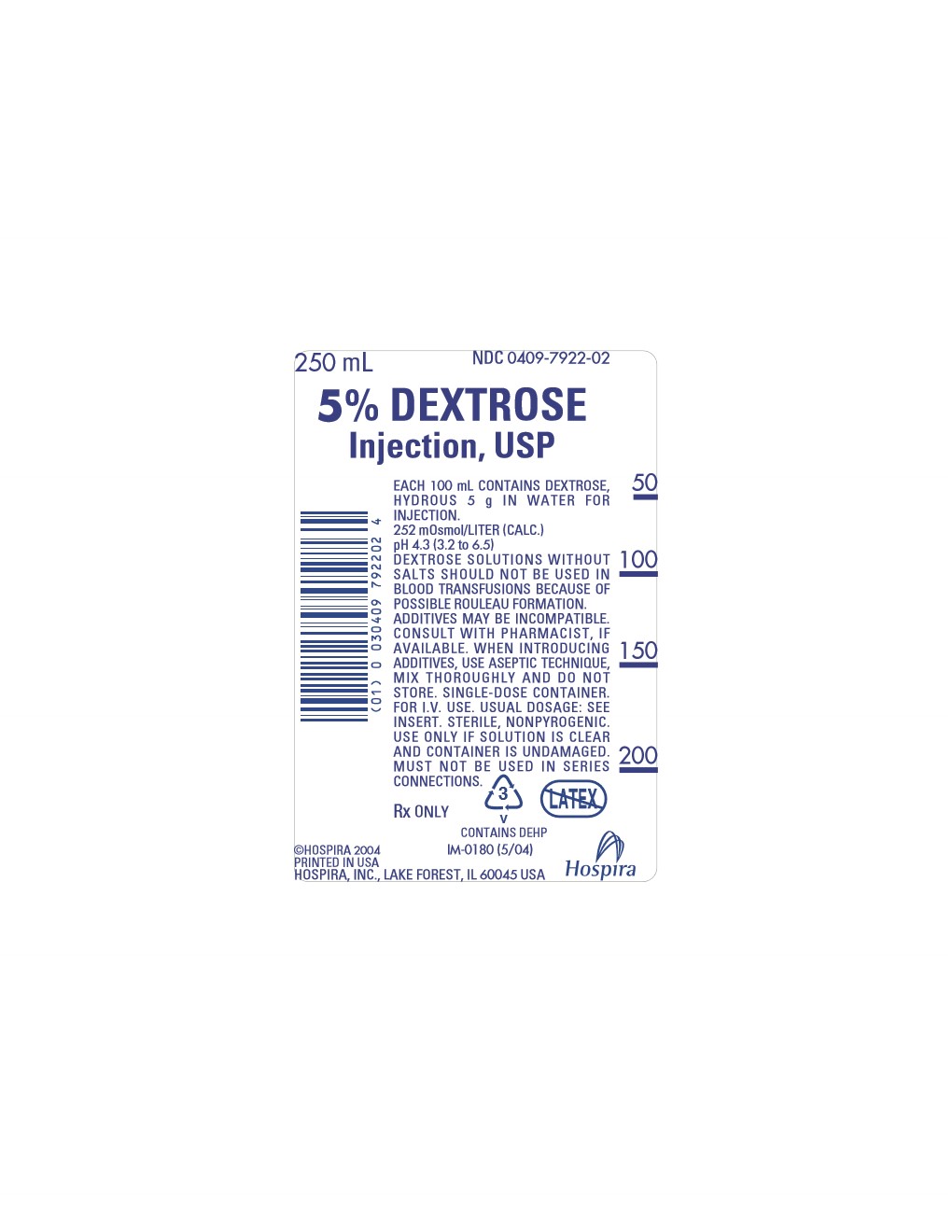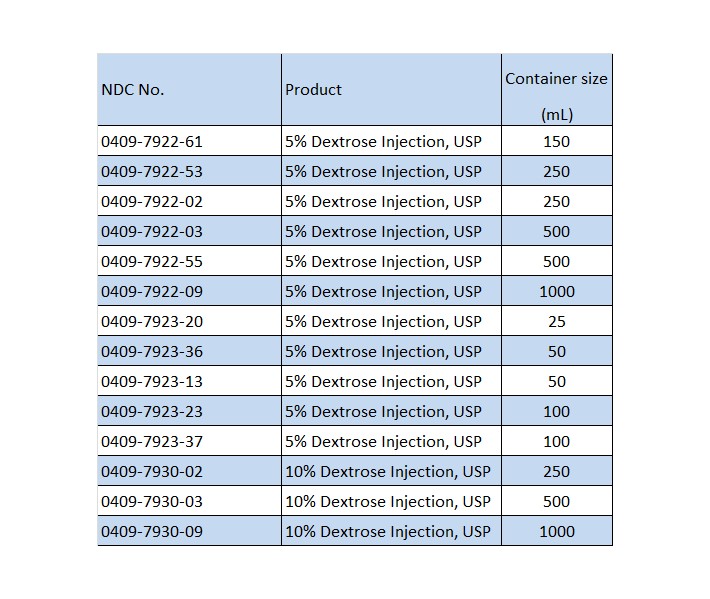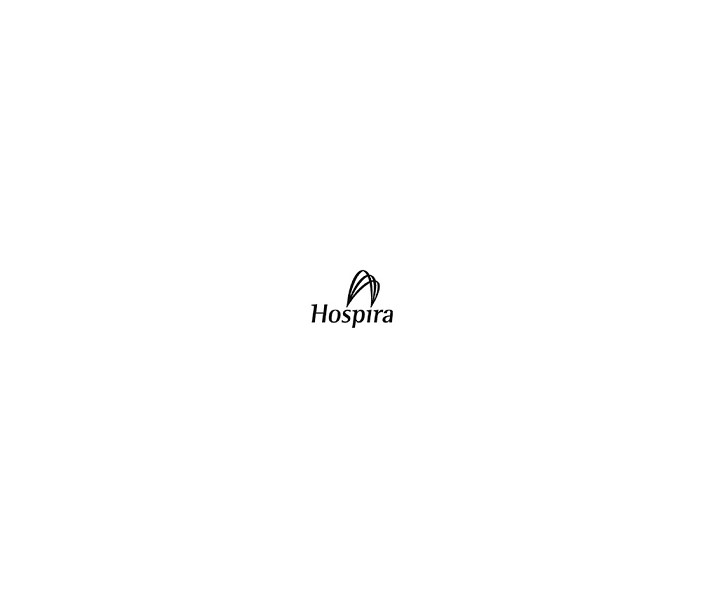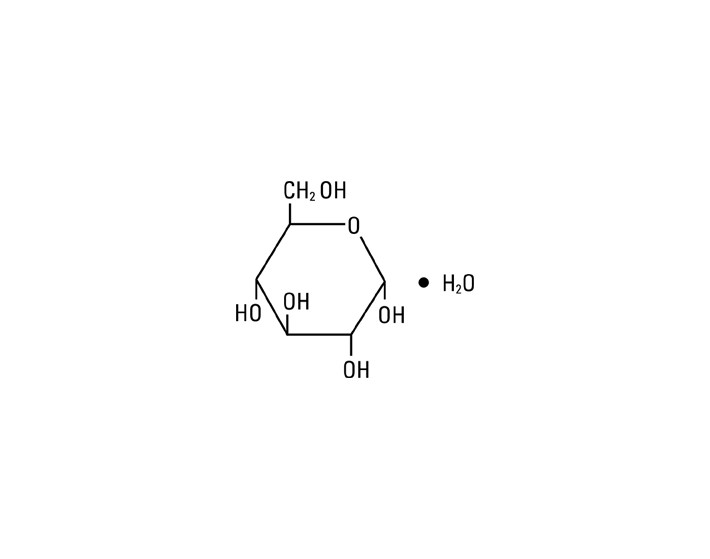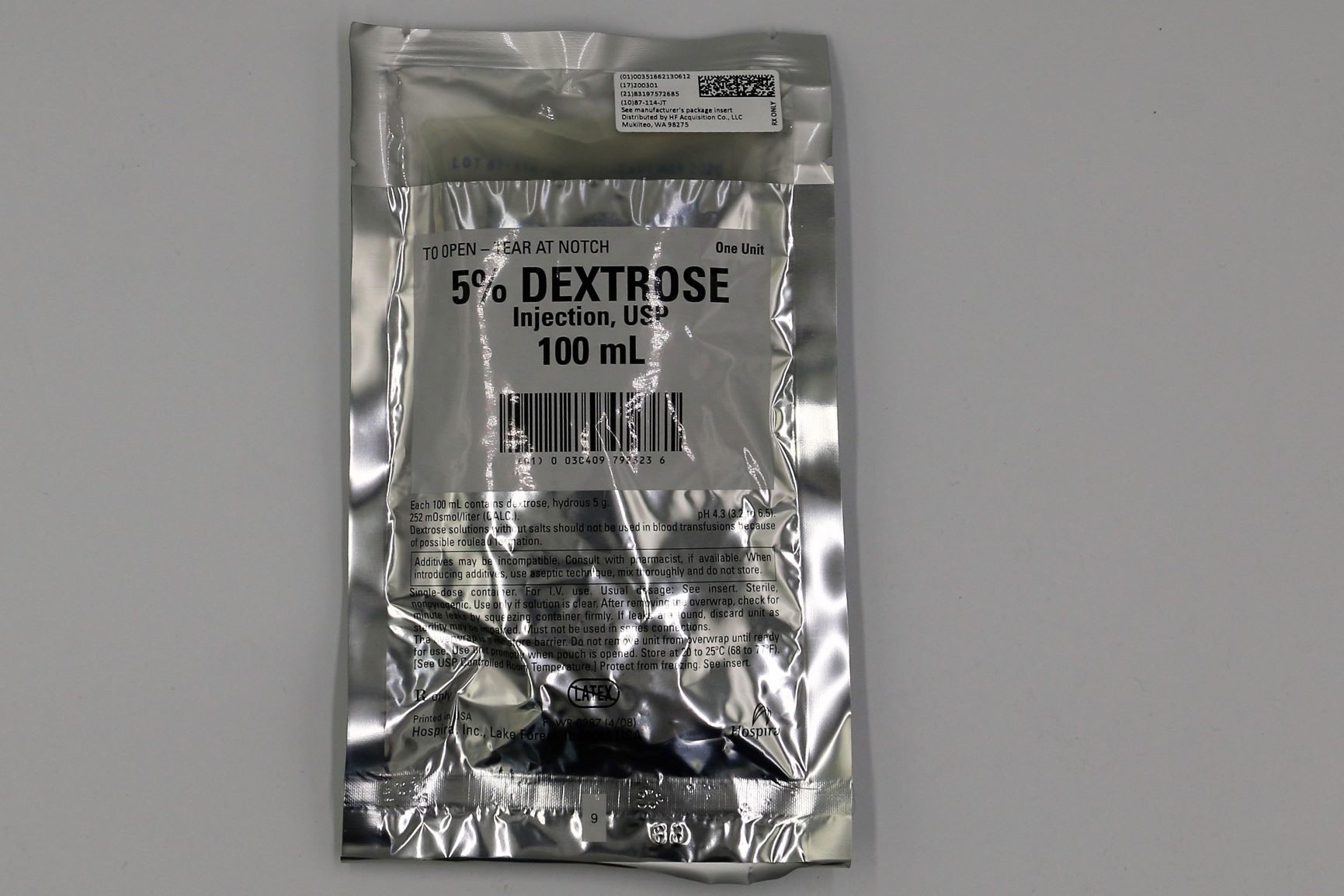 DRUG LABEL: DEXTROSE
NDC: 51662-1214 | Form: INJECTION, SOLUTION
Manufacturer: HF Acquisition Co LLC, DBA HealthFirst
Category: prescription | Type: HUMAN PRESCRIPTION DRUG LABEL
Date: 20200227

ACTIVE INGREDIENTS: DEXTROSE MONOHYDRATE 5 g/100 mL
INACTIVE INGREDIENTS: WATER

5% DEXTROSE INJECTION

SPL UNCLASSIFIED

Dextrose Injection, USP
Flexible Plastic Container Rx only

DESCRIPTION

Dextrose Injection, USP solutions are sterile and nonpyrogenic. They are parenteral solutions containing various concentrations of dextrose in water for injection intended for intravenous administration.

Each 100 mL of 5% Dextrose Injection, USP, contains dextrose, hydrous 5 g in water for injection. The caloric value is 170 kcal/L. The osmolarity is 252 mOsmol/L (calc.), which is slightly hypotonic.

Each 100 mL of 10% Dextrose Injection, USP, contains dextrose, hydrous 10 g in water for injection. The caloric value is 340 kcal/L. The osmolarity is 505 mOsmol/L (calc.), which is hypertonic.

The pH for both concentrations is 4.3 (3.2 to 6.5).

The solutions contain no bacteriostat, antimicrobial agent or added buffer and each is intended only as a single-dose injection. When smaller doses are required the unused portion should be discarded.

The solutions are parenteral fluid and nutrient replenishers.

Dextrose, USP is chemically designated D-glucose monohydrate (C6H12O6 • H2O), a hexose sugar freely soluble in water. It has the following structural formula:

Water for Injection, USP is chemically designated H2O.

The flexible plastic container is fabricated from a specially formulated polyvinylchloride. Water can permeate from inside the container into the overwrap but not in amounts sufficient to affect the solution significantly. Solutions in contact with the plastic container may leach out certain chemical components from the plastic in very small amounts; however, biological testing was supportive of the safety of the plastic container materials. Exposure to temperatures above 25°C/77°F during transport and storage will lead to minor losses in moisture content. Higher temperatures lead to greater losses. It is unlikely that these minor losses will lead to clinically significant changes within the expiration period.

CLINICAL PHARMACOLOGY

When administered intravenously, these solutions provide a source of water and carbohydrate.

Isotonic and hypertonic concentrations of dextrose are suitable for parenteral maintenance of water requirements when salt is not needed or should be avoided.

Solutions containing carbohydrate in the form of dextrose restore blood glucose levels and provide calories. Carbohydrate in the form of dextrose may aid in minimizing liver glycogen depletion and exerts a protein-sparing action. Dextrose injected parenterally undergoes oxidation to carbon dioxide and water.

Water is an essential constituent of all body tissues and accounts for approximately 70% of total body weight. Average normal adult daily requirements range from two to three liters (1.0 to 1.5 liters each for insensible water loss by perspiration and urine production).

Water balance is maintained by various regulatory mechanisms. Water distribution depends primarily on the concentration of electrolytes in the body compartments and sodium (Na+) plays a major role in maintaining physiologic equilibrium.

NDICATIONS & USAGE

Intravenous solutions containing dextrose are indicated for parenteral replenishment of fluid and minimal carbohydrate calories as required by the clinical condition of the patient.

CONTRAINDICATIONS

Dextrose Injection without electrolytes should not be administered simultaneously with blood through the same infusion set because of the possibility that pseudoagglutination of red cells may occur.

WARNINGS

Excessive administration of potassium-free solutions may result in significant hypokalemia.

The intravenous administration of these solutions can cause fluid and/or solute overloading resulting in dilution of serum electrolyte concentrations, overhydration, congested states or pulmonary edema.

The risk of dilutional states is inversely proportional to the electrolyte concentrations of administered parenteral solutions. The risk of solute overload causing congested states with peripheral and pulmonary edema is directly proportional to the electrolyte concentrations of such solutions.

PRECAUTIONS

Clinical evaluation and periodic laboratory determinations are necessary to monitor changes in fluid balance, electrolyte concentrations and acid-base balance during prolonged parenteral therapy or whenever the condition of the patient warrants such evaluation.

Solutions containing dextrose should be used with caution in patients with known subclinical or overt diabetes mellitus.

Do not administer unless solution is clear and container is undamaged. Discard unused portion.

Carcinogenesis, Mutagenesis, Impairment of Fertility: Studies with Dextrose Injection, USP have not been performed to evaluate carcinogenic potential, mutagenic potential or effects on fertility.

Pregnancy: Teratogenic effects

Pregnancy Category C. Animal reproduction studies have not been conducted with dextrose. It is also not known whether dextrose can cause fetal harm when administered to a pregnant woman or can affect reproduction capacity. Dextrose should be given to a pregnant woman only if clearly needed.

Nursing Mothers: Caution should be exercised when Dextrose Injection, USP is administered to a nursing mother.

Pediatric Use: The safety and effectiveness in the pediatric population are based on the similarity of the clinical conditions of the pediatric and adult populations. In neonates or very small infants the volume of fluid may affect fluid and electrolyte balance.

Frequent monitoring of serum glucose concentrations is required when dextrose is prescribed to pediatric patients, particularly neonates and low birth weight infants.

In very low birth weight infants, excessive or rapid administration of dextrose injection may result in increased serum osmolarity and possible intracerebral hemorrhage.

Geriatric Use: An evaluation of current literature revealed no clinical experience identifying differences in response between elderly and younger patients. In general, dose selection for an elderly patient should be cautious, usually starting at the low end of the dosing range, reflecting the greater frequency of decreased hepatic, renal, or cardiac function, and of concomitant disease or other drug therapy.

ADVERSE REACTIONS

Reactions which may occur because of the solution or the technique of administration include febrile response, infection at the site of injection, venous thrombosis or phlebitis extending from the site of injection, extravasation and hypervolemia.

If an adverse reaction does occur, discontinue the infusion, evaluate the patient, institute appropriate therapeutic countermeasures and save the remainder of the fluid for examination if deemed necessary.

OVERDOSAGE

In the event of overhydration or solute overload, re-evaluate the patient and institute appropriate corrective measures. (See WARNINGS, PRECAUTIONS, and ADVERSE REACTIONS.)

DOSAGE & ADMINISTRATION

he dose is dependent upon the age, weight and clinical condition of the patient.

As reported in the literature, the dosage and constant infusion rate of intravenous dextrose must be selected with caution in pediatric patients, particularly neonates and low birth weight infants, because of the increased risk of hyperglycemia/hypoglycemia.

Drug Interactions

Additives may be incompatible. Consult with pharmacist, if available. When introducing additives, use aseptic technique, mix thoroughly and do not store.

Parenteral drug products should be inspected visually for particulate matter and discoloration prior to administration, whenever solution and container permit. (See PRECAUTIONS.)

INSTRUCTIONS FOR USE

To Open:

Tear outer wrap at notch and remove solution container. If supplemental medication is desired, follow directions below before preparing for administration.

To Add Medication

1.
Prepare additive port.
2.
Using aseptic technique and an additive delivery needle of appropriate length, puncture resealable additive port at target area, inner diaphragm and inject. Withdraw needle after injecting medication.
3.
The additive port may be protected by covering with an additive cap.
4.
Mix container contents thoroughly.

Preparation for Administration

(Use aseptic technique)

1.
Close flow control clamp of administration set.
2.
Remove cover from outlet port at bottom of container.
3.
Insert piercing pin of administration set into port with a twisting motion until the set is firmly seated. NOTE: When using a vented administration set, replace bacterial retentive air filter with piercing pin cover. Insert piercing pin with twisting motion until shoulder of air filter housing rests against the outlet port flange.
4.
Suspend container from hanger.
5.
Squeeze and release drip chamber to establish proper fluid level in chamber.
6.
Attach venipuncture device to set.
7.
Open clamp to expel air from set and venipuncture device. Close clamp.
8.
Perform venipuncture.
9.
Regulate rate of administration with flow control clamp.

WARNING: Do not use flexible container in series connections.

HOW SUPPLIED

5% DEXTROSE INJECTION is supplied in the following dosage forms.
NDC 51662-1214-1
5% DEXTROSE INJECTION, USP 250mL BAG

NDC 51662-1306-1

5% DEXTROSE INJECTION, USP 100mL BAG

HF Acquisition Co LLC, DBA HealthFirst
Mukilteo, WA 98275

Also supplied in the following manufactures dosage forms

Dextrose Injection, USP is supplied in single-dose flexible plastic containers in various sizes and concentrations as shown in the accompanying Table.

Store at 20 to 25°C (68 to 77°F). [See USP Controlled Room Temperature.] Protect from freezing.

Revised: June, 2010

Printed in USA EN-2531

Hospira, Inc., Lake Forest, IL 60045 USA

PRINCIPAL DISPLAY PANEL, 100 mL SERIALIZED

100mL Serialized Bag